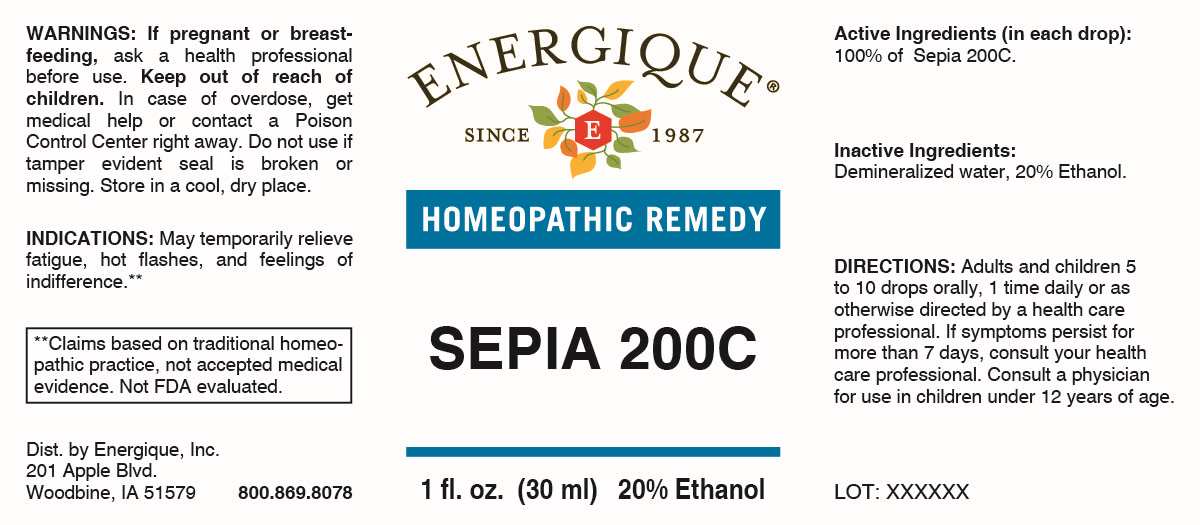 DRUG LABEL: Sepia
NDC: 44911-0391 | Form: LIQUID
Manufacturer: Energique, Inc.
Category: homeopathic | Type: HUMAN OTC DRUG LABEL
Date: 20250429

ACTIVE INGREDIENTS: SEPIA OFFICINALIS JUICE 200 [hp_C]/1 mL
INACTIVE INGREDIENTS: WATER; ALCOHOL

DRUG FACTS:

ACTIVE INGREDIENT:

(in each drop): 100% of Sepia 200C.

PURPOSE:

May temporarily relieve fatigue, hot flashes, and feelings of indifference.**

**Claims based on traditional homeopathic practice, not accepted medical evidence. Not FDA evaluated.

WARNINGS:

If pregnant or breastfeeding, ask a health professional before use.

Keep out of reach of children. In case of overdose, get medical help or contact a Poison Control Center right away.

Do not use if tamper evident seal is broken or missing.

Store in a cool, dry place.

KEEP OUT OF REACH OF CHILDREN:

In case of overdose, get medical help or contact a Poison Control Center right away.

DIRECTIONS:

Adults and children 5 to 10 drops orally, 1 time daily or as otherwise directed by a health care professional. If symptoms persist for more than 7 days, consult your health care professional. Consult a physician for use in children under 12 years of age.

INDICATIONS:

May temporarily relieve fatigue, hot flashes, and feelings of indifference.**

**Claims based on traditional homeopathic practice, not accepted medical evidence. Not FDA evaluated.

INACTIVE INGREDIENTS:

Demineralized water, 20% Ethanol.

QUESTIONS:

Dist. by Energique, Inc.
201 Apple Blvd.
Woodbine, IA 51579

800.868.8078

PACKAGE LABEL DISPLAY:

ENERGIQUE

SINCE 1987

HOMEOPATHIC REMEDY

SEPIA 200C

1 fl. oz. (30 ml)